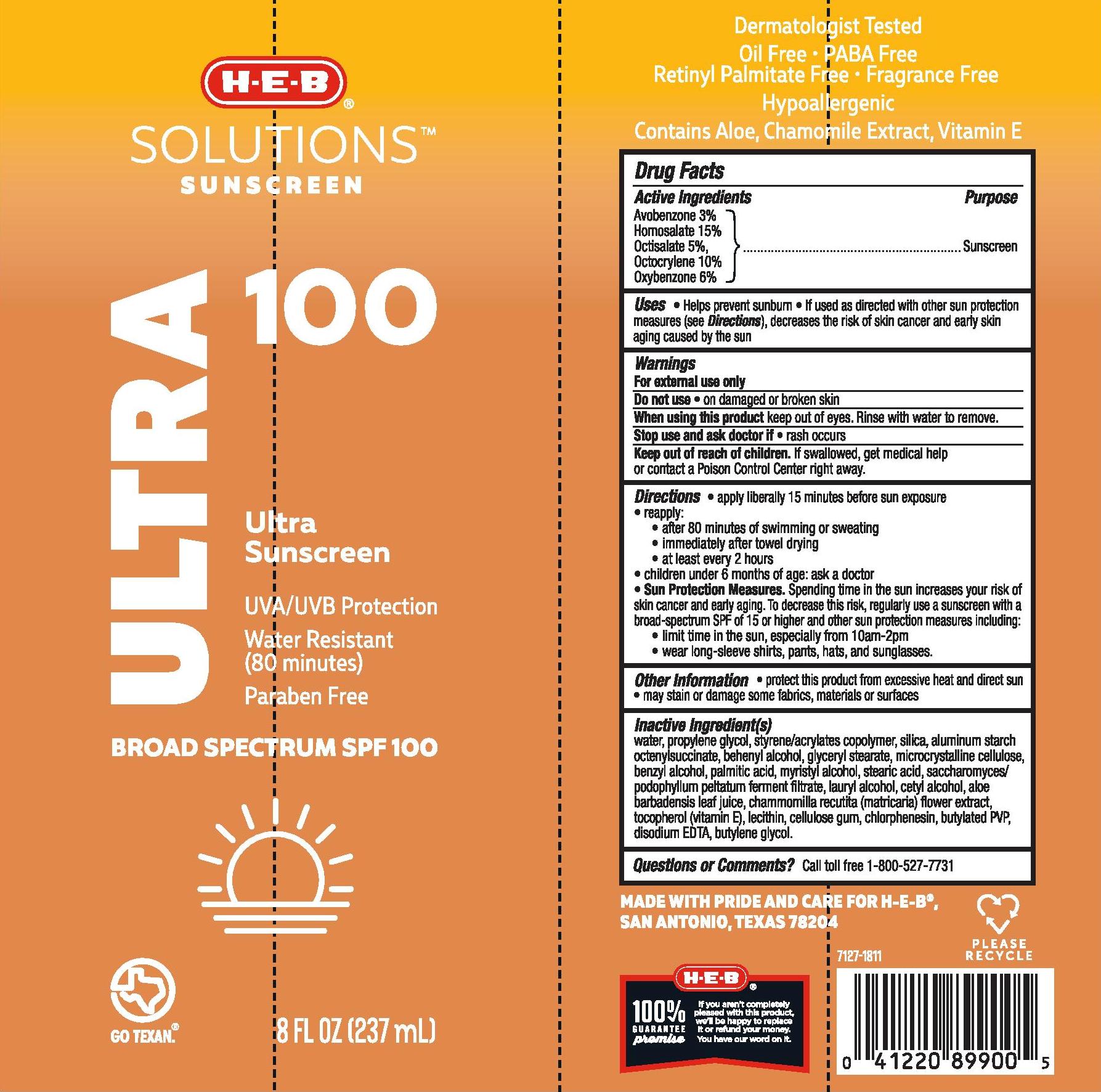 DRUG LABEL: HEB
NDC: 37808-943 | Form: LOTION
Manufacturer: H-E-B
Category: otc | Type: HUMAN OTC DRUG LABEL
Date: 20241015

ACTIVE INGREDIENTS: AVOBENZONE 30 mg/1 mL; HOMOSALATE 150 mg/1 mL; OCTISALATE 50 mg/1 mL; OCTOCRYLENE 100 mg/1 mL; OXYBENZONE 60 mg/1 mL
INACTIVE INGREDIENTS: WATER; EDETATE DISODIUM; PROPYLENE GLYCOL; SILICON DIOXIDE; ALUMINUM STARCH OCTENYLSUCCINATE; DOCOSANOL; GLYCERYL MONOSTEARATE; MICROCRYSTALLINE CELLULOSE; BENZYL ALCOHOL; PALMITIC ACID; MYRISTYL ALCOHOL; STEARIC ACID; LAURYL ALCOHOL; CETYL ALCOHOL; ALOE VERA LEAF; CHAMOMILE; TOCOPHEROL; LECITHIN, SOYBEAN; CARBOXYMETHYLCELLULOSE SODIUM; CHLORPHENESIN; BUTYLENE GLYCOL; N-VINYLPYRROLIDINONE

HEB Solutions Sunscreen Ultra 100 Lotion

Active Ingredients

Avobenzone 3%, Homosalate 15%, Octisalate 5%, Octocrylene 10%, Oxybenzone 6%

Purpose

Sunscreen

Uses

- Helps prevent sunburn
- If used as directed with other sun protection measures (see Directions), decreases the risk of skin cancer and early skin aging caused by the sun

Warnings

For external use only

Do not use • on damaged or broken skin.

When using this product keep out of eyes. Rinse with water to remove.

Stop use and ask doctorif • rash occurs.

Keep out of reach of children. If swallowed, get medical help or contact a Poison Control Center right away.

Directions

- apply liberally 15 minutes before sun exposure
- reapply:
- after 80 minutes of swimming or sweating
- Immediately after towel drying
- at least every 2 hours
- children under 6 months of age: ask a doctor
- Sun Protection Measures. Spending time in the sun increases your risk of skin cancer and early aging. To decrease this risk, regularly use a sunscreen with a broad-spectrum SPF of 15 or higher and other sun protection measures including:
- limit time in the sun especially from 10 a.m. – 2 p.m.
- wear long-sleeve shirts, pants, hats, and sunglasses.

Other information

- protect this product from excessive heat and direct sun
- may stain or damage some fabrics, materials or surfaces

Inactive ingredients

water, propylene glycol, styrene/acrylates copolymer, silica, aluminum starch octenylsuccinate, behenyl alcohol, glyceryl stearate, microcrystalline cellulose, benzyl alcohol, palmitic acid, myristyl alcohol, stearic acid, saccharomyces/podophyllum peltatum ferment filtrate, lauryl alcohol, cetyl alcohol, aloe barbadensis leaf juice, chamomilla recutita (matricaria) flower extract, tocopherol (vitamin E), lecithin, cellulose gum, chlorphenesin, butylated PVP, disodium EDTA, butylene glycol

PACKAGE LABEL

HEB Solutions Sunscreen Ultra 100 Lotion

8 FL OZ (237)

NDC 37808-943-12